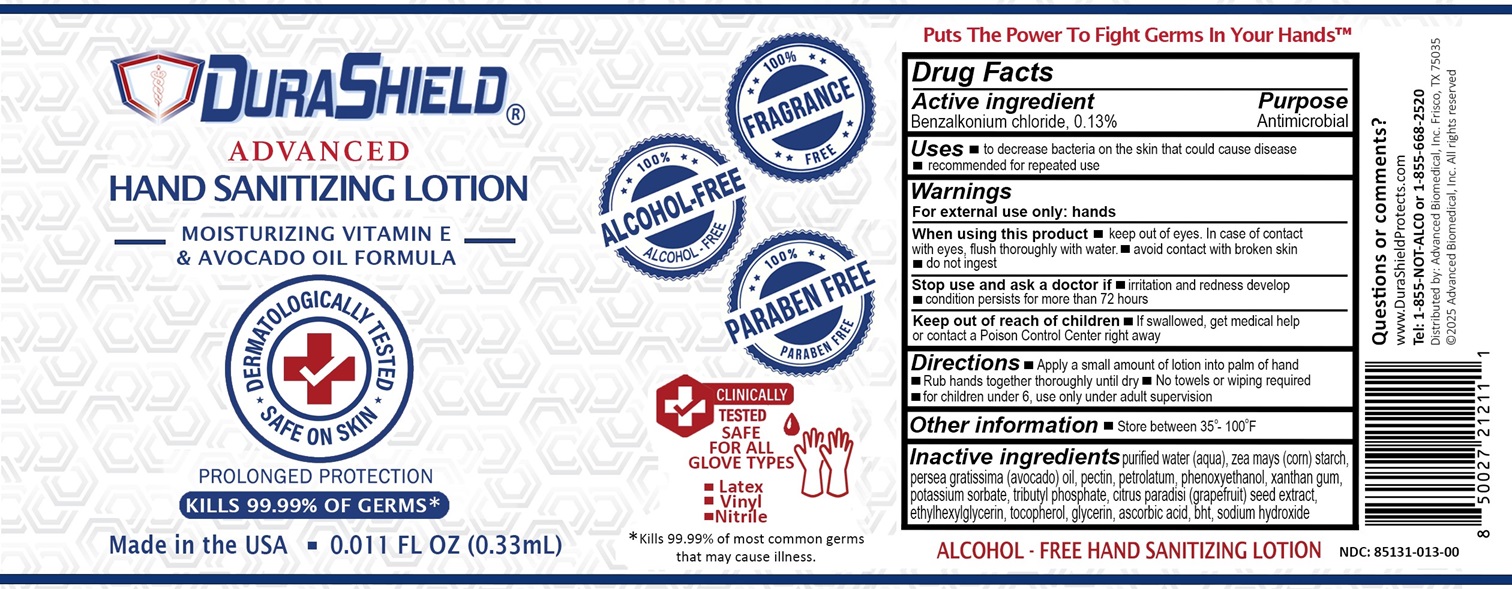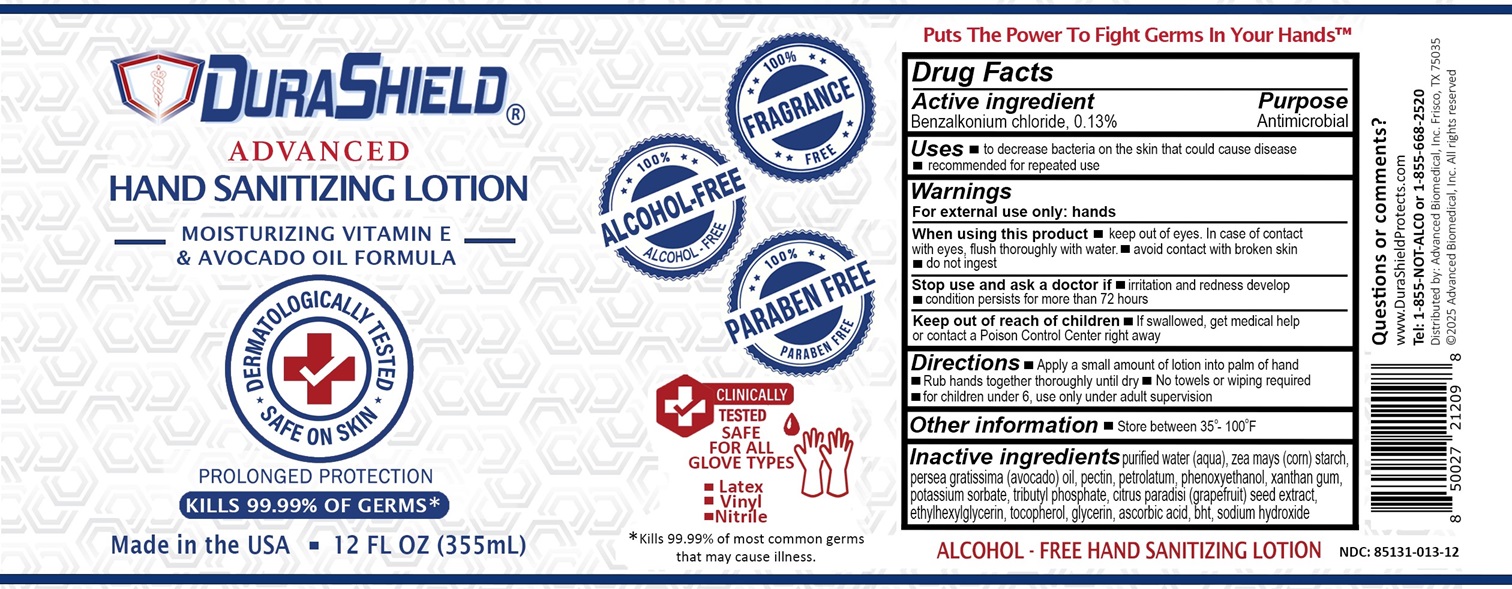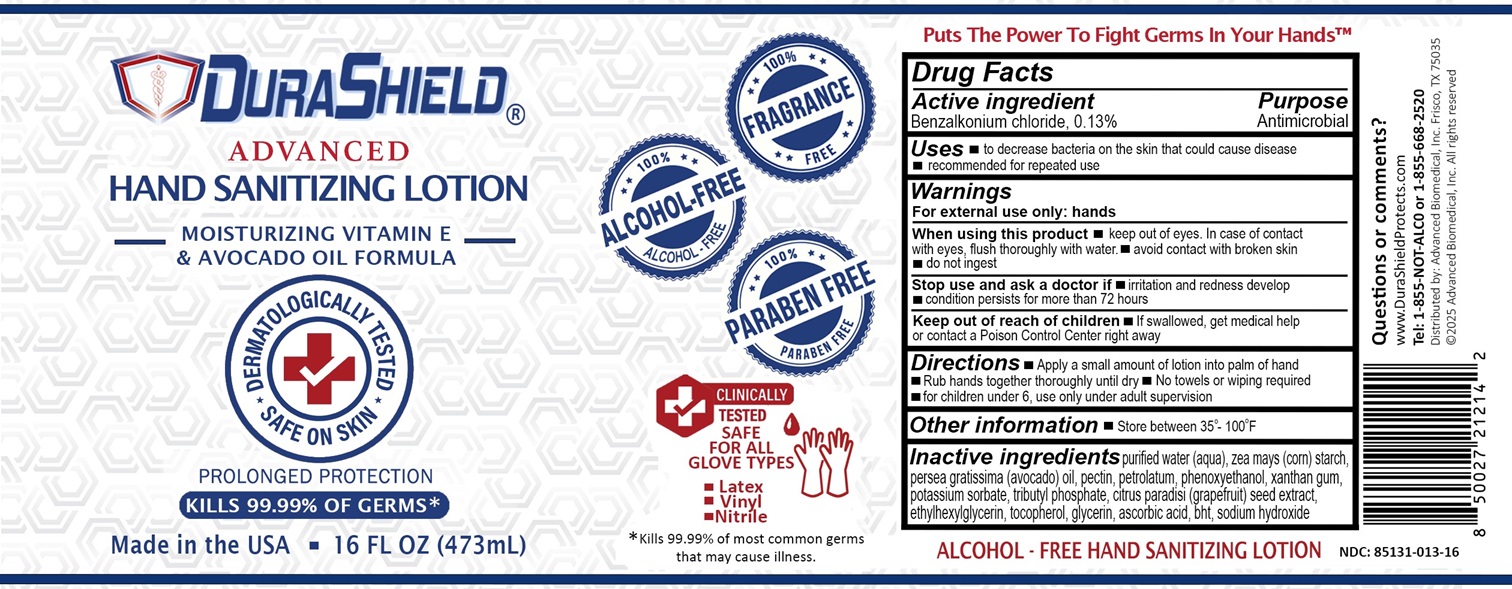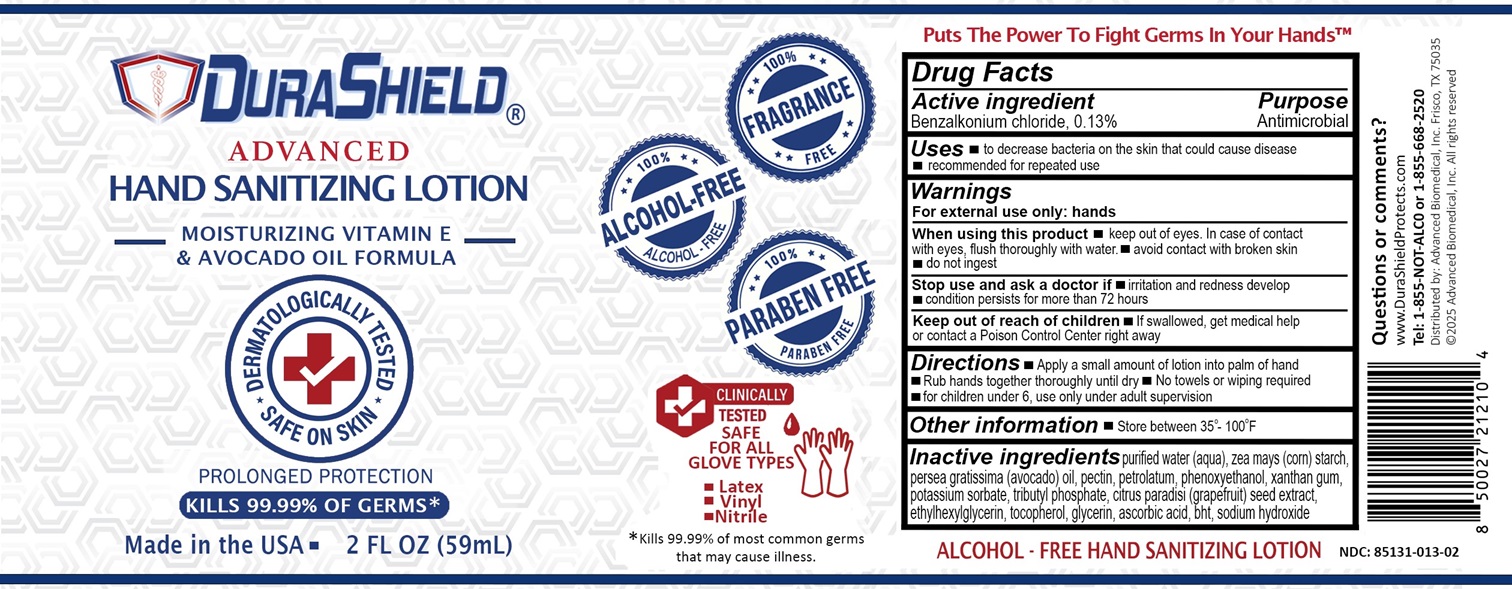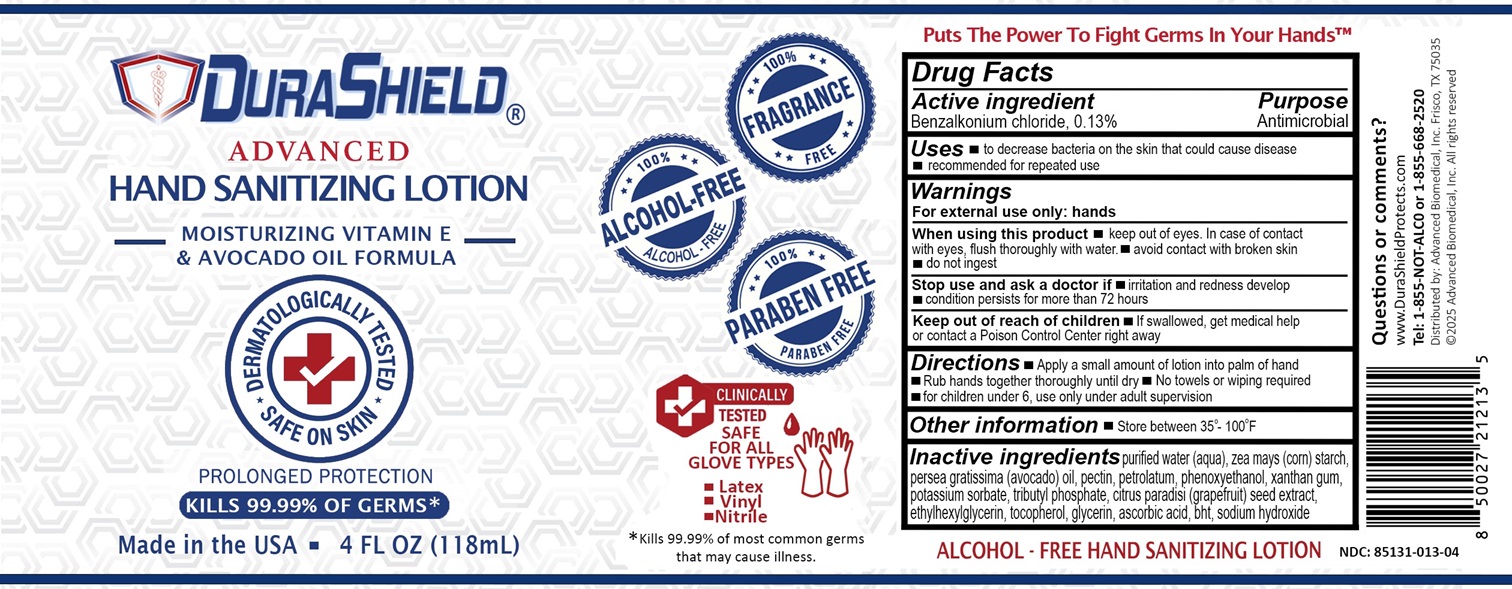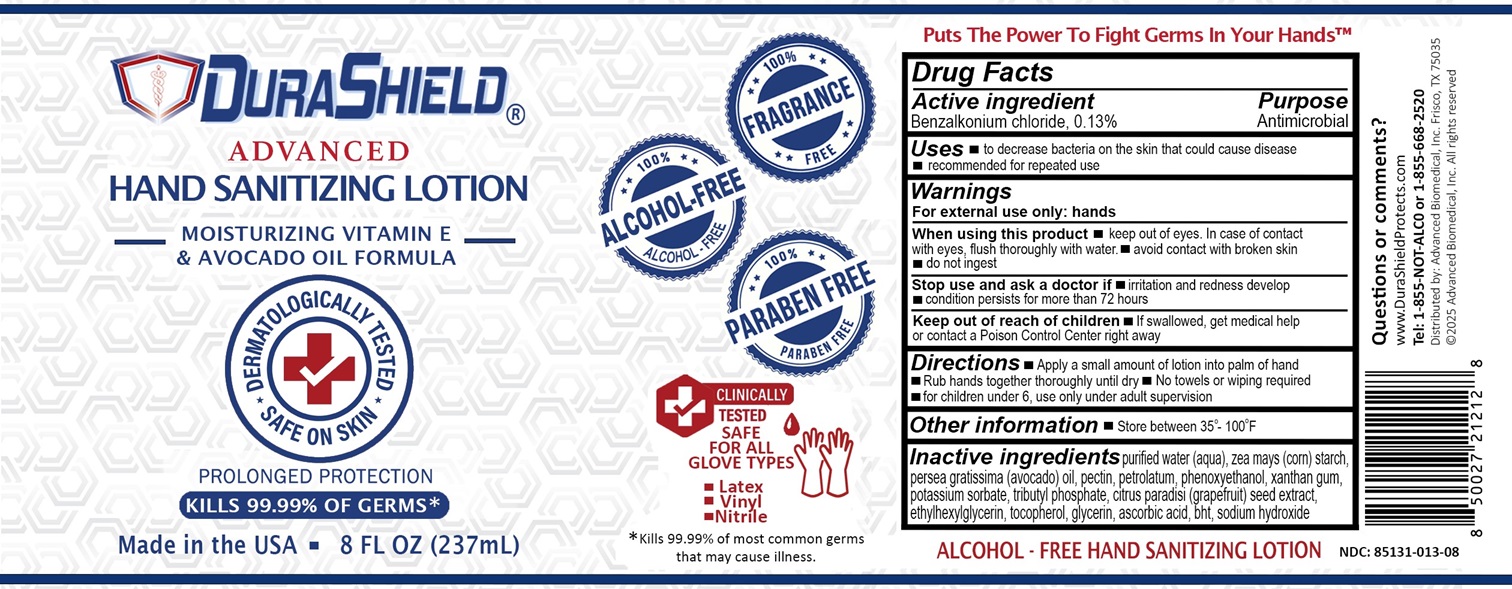 DRUG LABEL: Durashield
NDC: 85131-013 | Form: LOTION
Manufacturer: Advanced Biomedical Incorporated
Category: otc | Type: HUMAN OTC DRUG LABEL
Date: 20241218

ACTIVE INGREDIENTS: BENZALKONIUM CHLORIDE 0.13 mg/1 mL
INACTIVE INGREDIENTS: WATER; STARCH, CORN; AVOCADO OIL; PECTIN; PETROLATUM; PHENOXYETHANOL; XANTHAN GUM; POTASSIUM SORBATE; TRI-N-BUTYL PHOSPHATE; CITRUS PARADISI SEED; ETHYLHEXYLGLYCERIN; TOCOPHEROL; GLYCERIN; ASCORBIC ACID; BHT; SODIUM HYDROXIDE

Active ingredient

Benzalkonium chloride, 0.13%

Purpose

Antimicrobial

Uses

- to decrease bacteria on the skin that could cause disease
- recommended for repeated use

Warnings

For external use only: hands

When using this product

- keep out of eyes. In case of contact with eyes, flush thoroughly with water.
- avoid contact with broken skin
- do not ingest

Stop use and ask a doctor if

- irritation and redness develop
- condition persists for more than 72 hours

Keep out of reach of children

- If swallowed, get medical help or contact a Poison Control Center right away

Directions

- Apply a small amount of lotion into palm of hand
- Rub hands together thoroughly until dry
- No towels or wiping required
- for children under 6, use only under adult supervision

Other information

- Store between 35°-100°F

Inactive ingredients

purified water (aqua), zea mays (corn) starch, persea gratissima (avocado) oil, pectin, petrolatum, phenoxyethanol, xanthan gum, potassium sorbate, tributyl phosphate, citrus paradisi (grapefruit) seed extract, ethylhexylglycerin, tocopherol, glycerin, ascorbic acid, bht, sodium hydroxide

Questions or comments?

www.DuraShieldProtects.com
Tel: 1-855-NOT-ALC0 or 1-855-668-2520

Durashield Hand Sanitizing Lotion 0.011 Fl Oz - NDC 85131-013-00

DuraShield®

Advanced Hand Sanitizing Lotion

Moisturizing Vitamin E & Avocado Oil Formula

Dermatologically Tested

Safe on Skin

Prolonged Protection

Kills 99.99% of Germs*

Made in the USA

0.011 FL OZ (0.33mL)

100% Fragrance Free

100% Alcohol-Free

100% Paraben-Free

Clinically Tested

Safe for all glove types

- Latex
- Vinyl
- Nitrile

*Kills 99.99% of most common germs that may cause illness.

Puts The Power To Fight Germs In Your Hands™

Alcohol-Free Hand Sanitizing Lotion

NDC: 85131-013-00

Distributed by: Advanced Biomedical, Inc. Frisco, TX 75035

© 2025 Advanced Biomedical, Inc. All rights reserved.

Durashield Hand Sanitizing Lotion 2 Fl Oz - NDC 85131-013-02

DuraShield®

Advanced Hand Sanitizing Lotion

Moisturizing Vitamin E & Avocado Oil Formula

Dermatologically Tested

Safe on Skin

Prolonged Protection

Kills 99.99% of Germs*

Made in the USA

2 FL OZ (59mL)

100% Fragrance Free

100% Alcohol-Free

100% Paraben-Free

Clinically Tested

Safe for all glove types

- Latex
- Vinyl
- Nitrile

*Kills 99.99% of most common germs that may cause illness.

Puts The Power To Fight Germs In Your Hands™

Alcohol-Free Hand Sanitizing Lotion

NDC: 85131-013-02

Distributed by: Advanced Biomedical, Inc. Frisco, TX 75035

© 2025 Advanced Biomedical, Inc. All rights reserved.

Durashield Hand Sanitizing Lotion 4 Fl Oz - NDC 85131-013-04

DuraShield®

Advanced Hand Sanitizing Lotion

Moisturizing Vitamin E & Avocado Oil Formula

Dermatologically Tested

Safe on Skin

Prolonged Protection

Kills 99.99% of Germs*

Made in the USA

4 FL OZ (118mL)

100% Fragrance Free

100% Alcohol-Free

100% Paraben-Free

Clinically Tested

Safe for all glove types

- Latex
- Vinyl
- Nitrile

*Kills 99.99% of most common germs that may cause illness.

Puts The Power To Fight Germs In Your Hands™

Alcohol-Free Hand Sanitizing Lotion

NDC: 85131-013-04

Distributed by: Advanced Biomedical, Inc. Frisco, TX 75035

© 2025 Advanced Biomedical, Inc. All rights reserved.

Durashield Hand Sanitizing Lotion 8 Fl Oz - NDC 85131-013-08

DuraShield®

Advanced Hand Sanitizing Lotion

Moisturizing Vitamin E & Avocado Oil Formula

Dermatologically Tested

Safe on Skin

Prolonged Protection

Kills 99.99% of Germs*

Made in the USA

8 FL OZ (237mL)

100% Fragrance Free

100% Alcohol-Free

100% Paraben-Free

Clinically Tested

Safe for all glove types

- Latex
- Vinyl
- Nitrile

*Kills 99.99% of most common germs that may cause illness.

Puts The Power To Fight Germs In Your Hands™

Alcohol-Free Hand Sanitizing Lotion

NDC: 85131-013-08

Distributed by: Advanced Biomedical, Inc. Frisco, TX 75035

© 2025 Advanced Biomedical, Inc. All rights reserved.

Durashield Hand Sanitizing Lotion 12 Fl Oz - NDC 85131-013-12

DuraShield®

Advanced Hand Sanitizing Lotion

Moisturizing Vitamin E & Avocado Oil Formula

Dermatologically Tested

Safe on Skin

Prolonged Protection

Kills 99.99% of Germs*

Made in the USA

12 FL OZ (355mL)

100% Fragrance Free

100% Alcohol-Free

100% Paraben-Free

Clinically Tested

Safe for all glove types

- Latex
- Vinyl
- Nitrile

*Kills 99.99% of most common germs that may cause illness.

Puts The Power To Fight Germs In Your Hands™

Alcohol-Free Hand Sanitizing Lotion

NDC: 85131-013-12

Distributed by: Advanced Biomedical, Inc. Frisco, TX 75035

© 2025 Advanced Biomedical, Inc. All rights reserved.

Durashield Hand Sanitizing Lotion 16 Fl Oz - NDC 85131-013-16

DuraShield®

Advanced Hand Sanitizing Lotion

Moisturizing Vitamin E & Avocado Oil Formula

Dermatologically Tested

Safe on Skin

Prolonged Protection

Kills 99.99% of Germs*

Made in the USA

16 FL OZ (473mL)

100% Fragrance Free

100% Alcohol-Free

100% Paraben-Free

Clinically Tested

Safe for all glove types

- Latex
- Vinyl
- Nitrile

*Kills 99.99% of most common germs that may cause illness.

Puts The Power To Fight Germs In Your Hands™

Alcohol-Free Hand Sanitizing Lotion

NDC: 85131-013-16

Distributed by: Advanced Biomedical, Inc. Frisco, TX 75035

© 2025 Advanced Biomedical, Inc. All rights reserved.